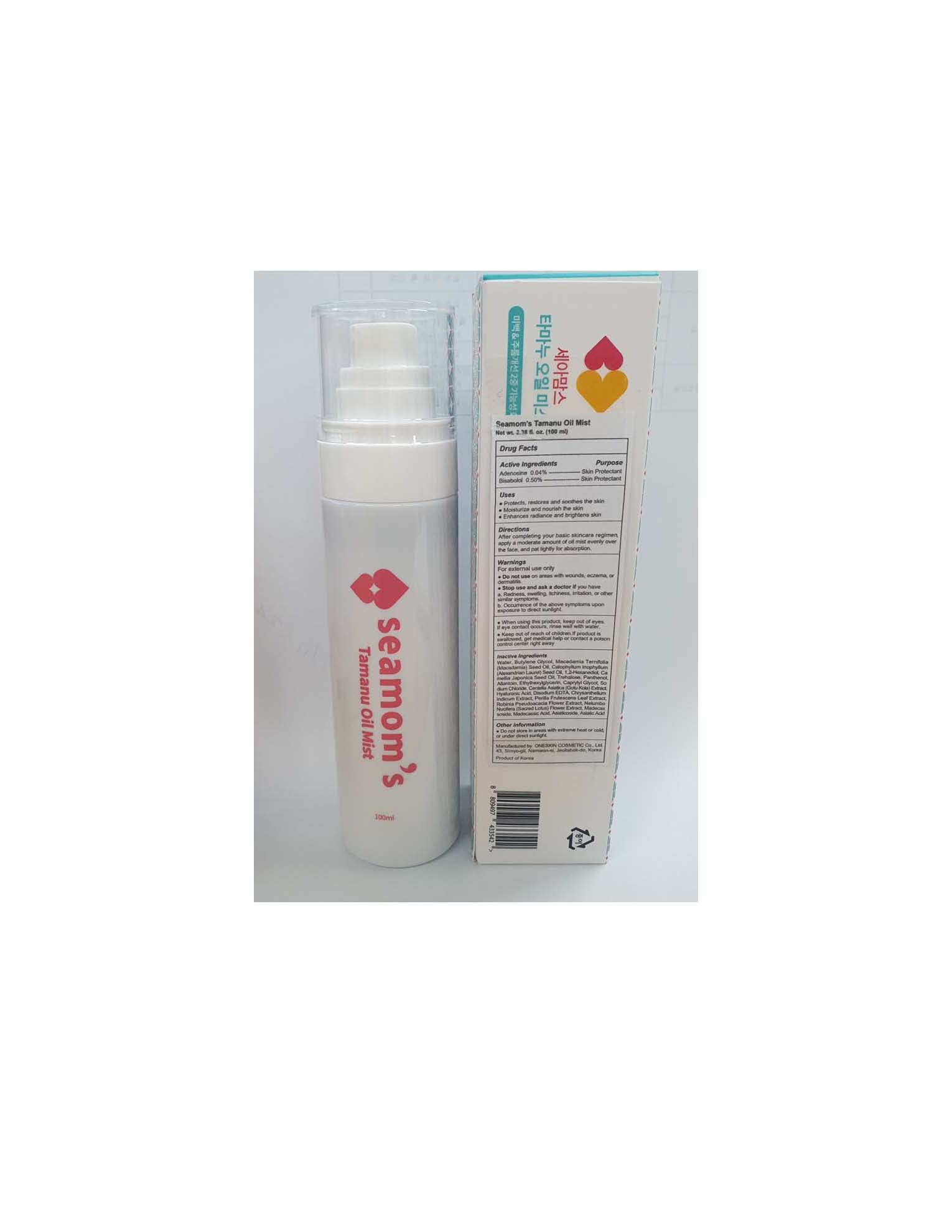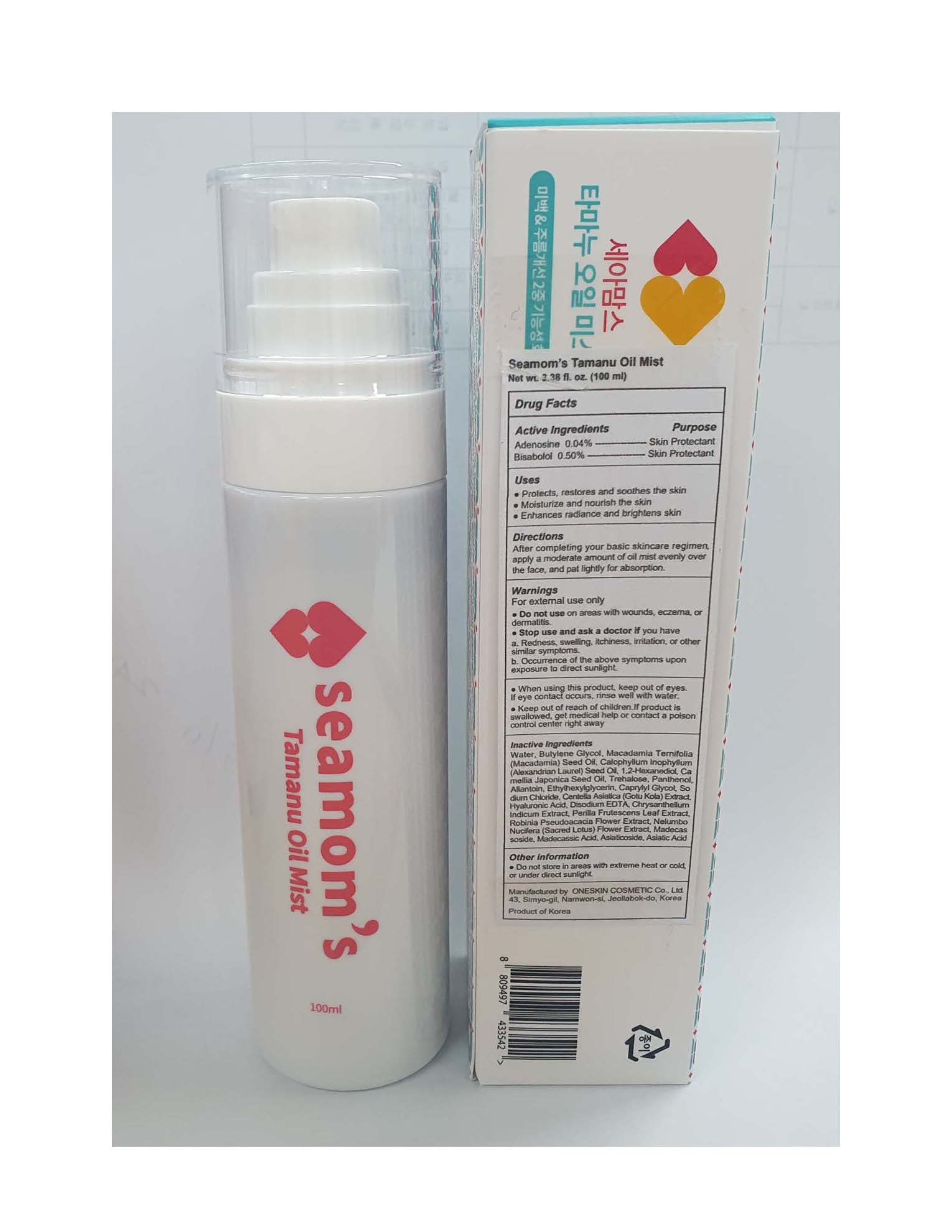 DRUG LABEL: Seamoms Tamanu Oil Mist
NDC: 70889-920 | Form: OIL
Manufacturer: Oneskin Cosmetics Co., Ltd.
Category: otc | Type: HUMAN OTC DRUG LABEL
Date: 20210127

ACTIVE INGREDIENTS: ADENOSINE 0.04 g/100 mL; LEVOMENOL 0.5 g/100 mL
INACTIVE INGREDIENTS: MACADAMIA OIL; WATER; BUTYLENE GLYCOL; ALLANTOIN; EDETATE DISODIUM

ACTIVE INGREDIENT

Bisabolol 0.50%

Adenosine 0.04%

PURPOSE

Skin Protectant

INDICATIONS AND USAGE

- Protects, restores and soothes the skin
- Moisturize and nourish the skin
- Enhances radiance and brightens skin

DOSAGE AND ADMINISTRATION

After completing your basic skincare regimen, apply a moderate amount of oil mist evenly over the face, and pat lightly for absorption.

WARNINGS

For external use only

- Do not use on areas with wounds, eczema, or dermatitis.
- Stop use and ask a doctor if you have

a. Redness, swelling, itchiness, irritation, or other similar symptoms.
b. Occurrence of the above symptoms upon exposure to direct sunlight.

- When using this product, keep out of eyes. If eye contact occurs, rinse well with water.
- Keep out of reach of children. If product is swallowed, get medical help or contact a poison control center right away

Keep out of reach of children. If product is swallowed, get medical help or contact a poison control center right away

INACTIVE INGREDIENT

Water, Butylene Glycol, Macadamia Ternifolia (Macadamia) Seed Oil, Calophyllum Inophyllum (Alexandrian Laurel) Seed Oil, 1,2-Hexanediol, Camellia Japonica Seed Oil, Trehalose, Panthenol, Allantoin, Ethylhexylglycerin, Caprylyl Glycol, Sodium Chloride, Centella Asiatica (Gotu Kola) Extract, Hyaluronic Acid, Disodium EDTA, Chrysanthellum Indicum Extract, Perilla Frutescens Leaf Extract, Robinia Pseudoacacia Flower Extract, Nelumbo Nucifera (Sacred Lotus) Flower Extract, Madecassoside, Madecassic Acid, Asiaticoside, Asiatic Acid.

OTHER SAFETY INFORMATION

- Do not store in areas with extreme heat or cold, or under direct sunlight.